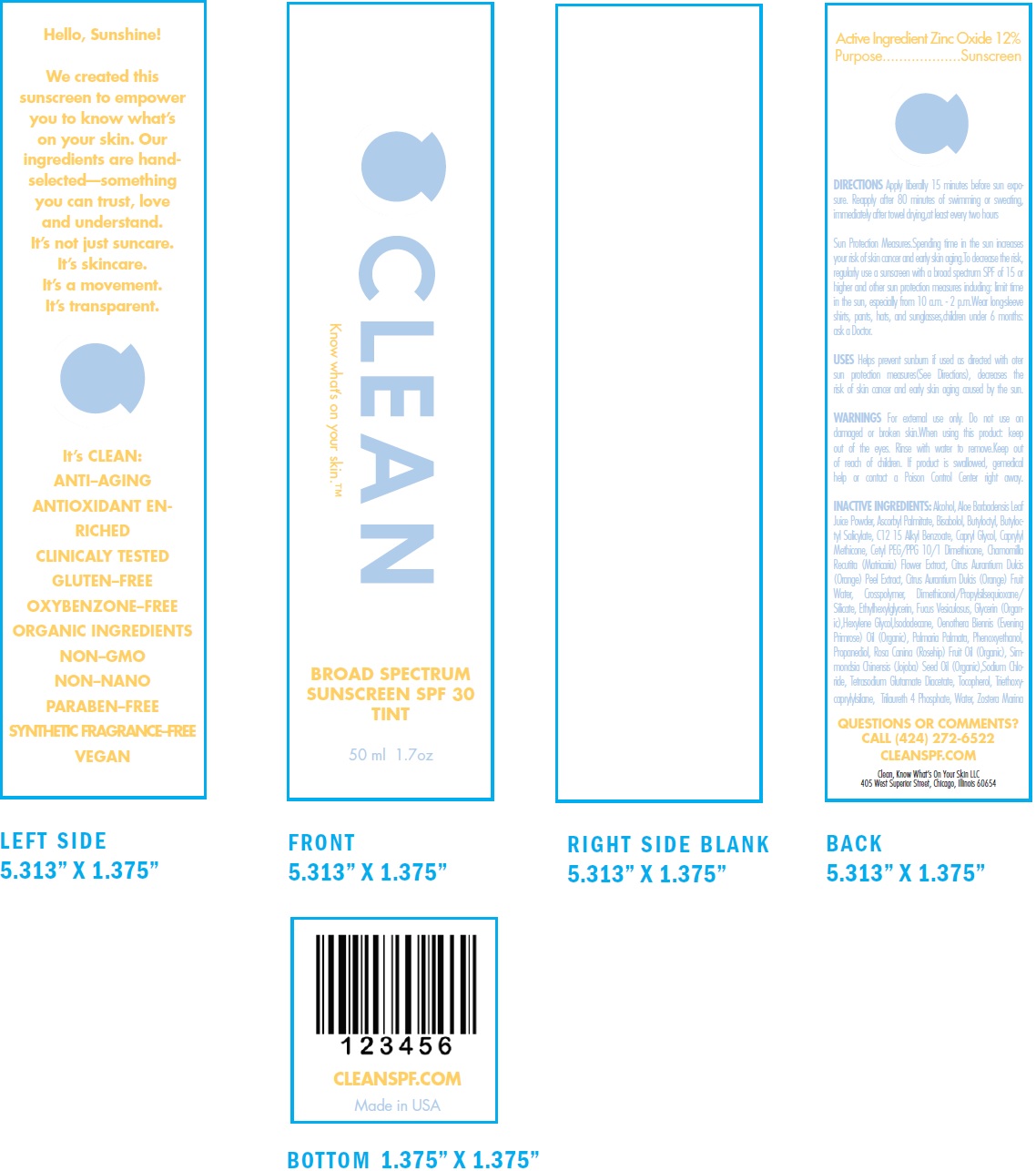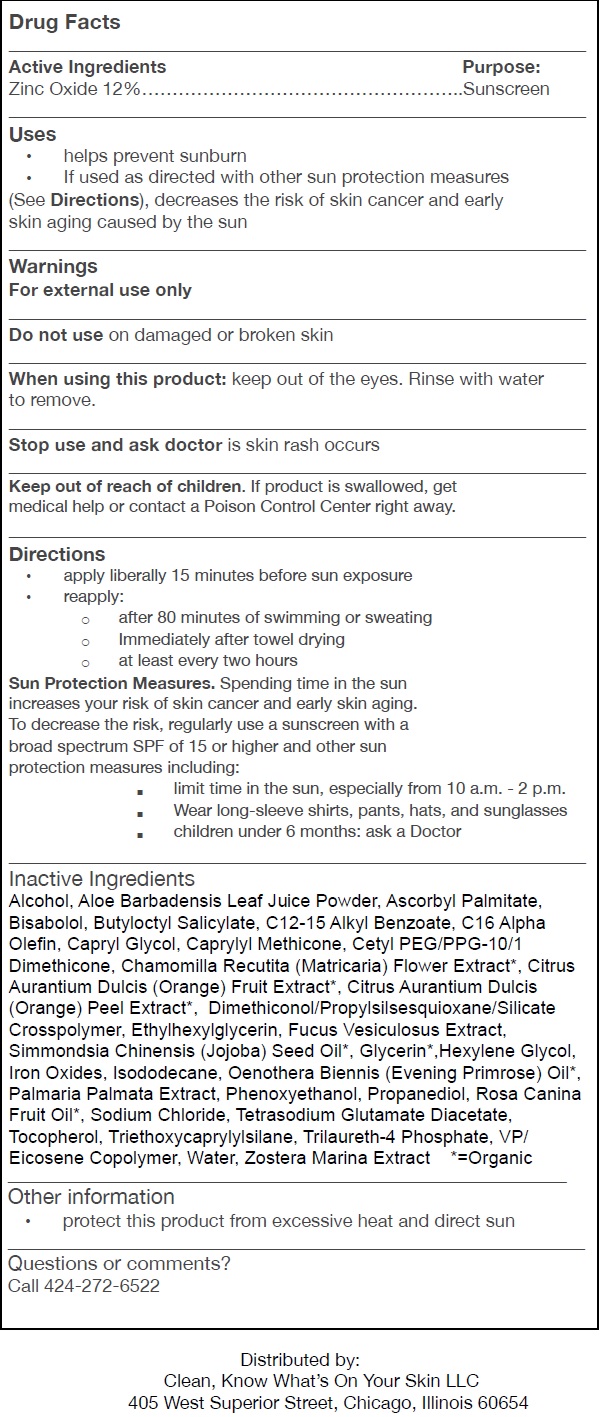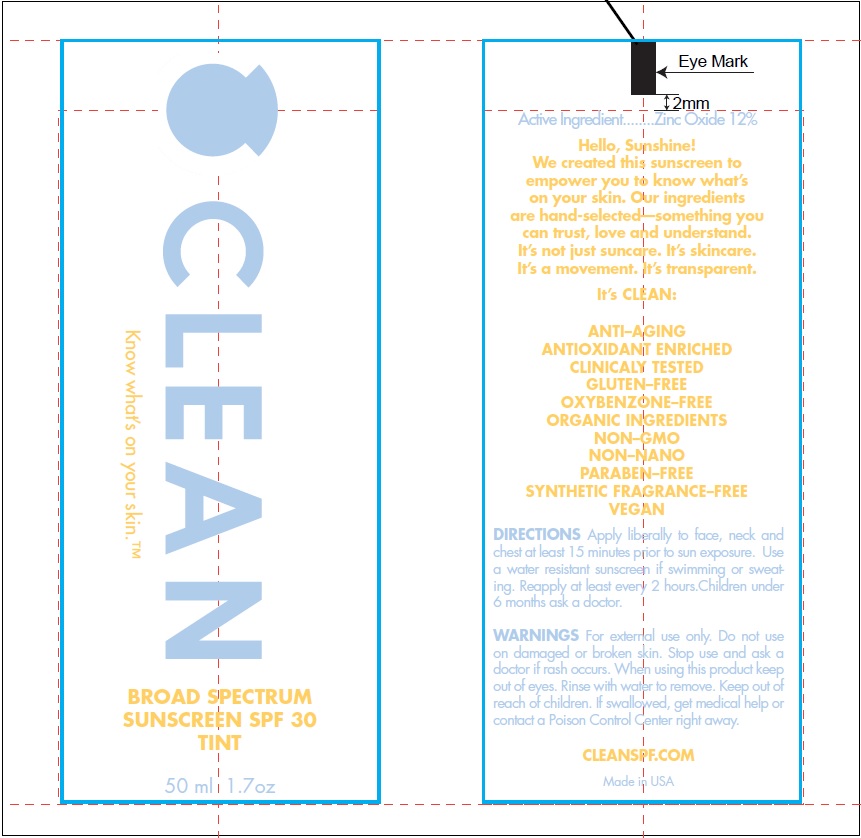 DRUG LABEL: Clean Tinted
NDC: 72394-001 | Form: LOTION
Manufacturer: Clean, Know What's On Your Skin LLC
Category: otc | Type: HUMAN OTC DRUG LABEL
Date: 20190329

ACTIVE INGREDIENTS: ZINC OXIDE 120 mg/1 mL
INACTIVE INGREDIENTS: ALCOHOL; ALOE VERA LEAF; ASCORBYL PALMITATE; LEVOMENOL; BUTYLOCTYL SALICYLATE; ALKYL (C12-15) BENZOATE; CAPRYLYL GLYCOL; CAPRYLYL TRISILOXANE; CHAMOMILE; ORANGE; ORANGE PEEL; ETHYLHEXYLGLYCERIN; GLYCERIN; HEXYLENE GLYCOL; FERRIC OXIDE RED; ISODODECANE; EVENING PRIMROSE OIL; DULSE; PHENOXYETHANOL; PROPANEDIOL; ROSA CANINA FRUIT OIL; SODIUM CHLORIDE; TETRASODIUM GLUTAMATE DIACETATE; TOCOPHEROL; TRIETHOXYCAPRYLYLSILANE; TRILAURETH-4 PHOSPHATE; WATER

Clean Tinted Lotion

Active Ingredients

Zinc Oxide 12%

Purpose:

Sunscreen

Uses

• helps prevent sunburn
• If used as directed with other sun protection measures (See Directions), decreases the risk of skin cancer and early skin aging caused by the sun

Warnings

For external use only

Do not use

on damaged or broken skin

When using this product:

keep out of the eyes. Rinse with water to remove.

Stop use and ask doctor

is skin rash occurs

Keep out of reach of children.

If product is swallowed, get medical help or contact a Poison Control Center right away.

Directions

• apply liberally 15 minutes before sun exposure
• reapply:
• after 80 minutes of swimming or sweating
• Immediately after towel drying
• at least every two hours
Sun Protection Measures. Spending time in the sun increases your risk of skin cancer and early skin aging. To decrease the risk, regularly use a sunscreen with a broad spectrum SPF of 15 or higher and other sun protection measures including:
• limit time in the sun, especially from 10 a.m. - 2 p.m.
• Wear long-sleeve shirts, pants, hats, and sunglasses
• children under 6 months: ask a Doctor

Inactive Ingredients

Alcohol, Aloe Barbadensis Leaf Juice Powder, Ascorbyl Palmitate, Bisabolol, Butyloctyl Salicylate, C12-15 Alkyl Benzoate, C16 Alpha Olefin, Capryl Glycol, Caprylyl Methicone, Cetyl PEG/PPG-10/1 Dimethicone, Chamomilla Recutita (Matricaria) Flower Extract*, Citrus Aurantium Dulcis (Orange) Fruit Extract*, Citrus Aurantium Dulcis (Orange) Peel Extract*, Dimethiconol/Propylsilsesquioxane/Silicate Crosspolymer, Ethylhexylglycerin, Fucus Vesiculosus Extract, Simmondsia Chinensis (Jojoba) Seed Oil*, Glycerin*,Hexylene Glycol, Iron Oxides, Isododecane, Oenothera Biennis (Evening Primrose) Oil*, Palmaria Palmata Extract, Phenoxyethanol, Propanediol, Rosa Canina Fruit Oil*, Sodium Chloride, Tetrasodium Glutamate Diacetate, Tocopherol, Triethoxycaprylylsilane, Trilaureth-4 Phosphate, VP/ Eicosene Copolymer, Water, Zostera Marina Extract *=Organic

Other information

• protect this product from excessive heat and direct sun

Questions or comments?

Call 424-272-6522